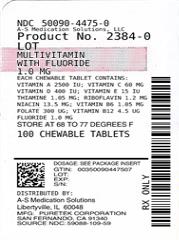 DRUG LABEL: Multivitamin with Fluoride
NDC: 50090-4475 | Form: TABLET, CHEWABLE
Manufacturer: A-S Medication Solutions
Category: prescription | Type: HUMAN PRESCRIPTION DRUG LABEL
Date: 20210302

ACTIVE INGREDIENTS: SODIUM FLUORIDE 1 mg/1 1; VITAMIN A 750 ug/1 1; ASCORBIC ACID 24 mg/1 1; SODIUM ASCORBATE 36 mg/1 1; CHOLECALCIFEROL 10 ug/1 1; .ALPHA.-TOCOPHEROL ACETATE, DL- 13.5 mg/1 1; THIAMINE MONONITRATE 1.05 mg/1 1; RIBOFLAVIN 1.2 mg/1 1; NIACIN 13.5 mg/1 1; PYRIDOXINE HYDROCHLORIDE 1.05 mg/1 1; FOLIC ACID 300 ug/1 1; CYANOCOBALAMIN 4.5 ug/1 1
INACTIVE INGREDIENTS: SUCROSE; CROSCARMELLOSE SODIUM; D&C RED NO. 27; FD&C BLUE NO. 1; MAGNESIUM STEARATE; MICROCRYSTALLINE CELLULOSE; STEARIC ACID; ASPARTAME

Multivitamin with Fluoride 1.0 mg
Prescribing Information

MULTIVITAMIN WITH FLUORIDE vitamin A, ascorbic acid, sodium ascorbate, cholecalciferol, alpha-tocopherol acetate, dl-, thiamine mononitrate, riboflavin, niacinamide, pyridoxine hydrochloride, folic acid and cyanocobalamin tablet, chewable

Each Fluoride Chewable Tablet Contains:

Supplement Facts

Dosage Size 1 Chewable Tablet

Amount per tablet 1.0 mg %DV Adults and Children 4 years or More

Vitamin A 750 ug 50%

Vitamin C 60 mg 100%

VItamin D 10 ug 100%

Vitamin E 13 mg 50%

Thiamine 1.05 mg 70%

Riboflavin 1.2 mg 71%

Niacin 13.5 mg 68%

Vitamin B6 1.05 mg 53%

Folate 300 ug 75%

Vitamin B12 4.5 ug 75%

Fluoride 1.0 mg *

*daily value (DV) not established

Multivitamin with Fluoride 1 mg active ingredient for caries prophylaxis: Fluoride as sodium fluoride

Multivitamin with 1 mg Fluoride Chewable Tablets

provide sodium fluoride and ten essential vitamins in a chewable tablet.

Other ingredients: ascorbic acid, cholecalciferol, compressible sugar, croscarmellose sodium, dl-alpha tocopheryl acetate, D and C Red #27 aluminum lake, FD and C Blue #1 aluminum lake, folic acid, grape flavor, magnesium stearate, microcrystalline cellulose, niacinamide, pyridoxine, riboflavin, sodium ascorbate, stearic acid, thiamine, vitamin A, vitamin B 12.

CLINICAL PHARMACOLOGY

It is well established that fluoridation of the water supply (1 ppm fluoride) during the period of tooth development leads to a significant decrease in the incidence of dental caries.

Multivitamin with 1.0 mg Fluoride Chewable Tablets provide sodium fluoride and ten essential vitamins in a chewable tablet. Because the tablets are chewable, they provide a topical as well as systemic source of fluoride.

Hydroxyapatite

is the principal crystal for all calcified tissue in the human body. The fluoride ion reacts with the hydroxyapatite in the tooth as it is formed to produce the more caries-resistant crystal,

fluorapatite

. The reaction may be expressed by the equation:

Ca 10(PO 4) 6(OH) 2 + 2F- ------- Ca 10(PO 4) 6F 2 + 2OH-

(Hydroxyapatite) (Fluorapatite)

Three stages of fluoride deposition in tooth enamel can be distinguished:

1. Small amounts (reflecting the low levels of fluoride in tissue fluids) are incorporated into the enamel crystals while they are being formed.

2. After enamel has been laid down, fluoride deposition continues in the surface enamel. Diffusion of fluoride from the surface inward is apparently restricted.

3. After eruption, the surface enamel acquires fluoride from the water, food, supplementary fluoride and smaller amounts from saliva.

INDICATIONS AND USAGE

Supplementation of the diet with ten essential vitamins.

Supplementation of the diet with fluoride for caries prophylaxis.

Multivitamin with 1.0 mg Fluoride Chewable Tablets

provide 1.0 mg fluoride in tablet form for children 6-16 years of age in areas where the water fluoride level is less than 0.3 ppm.

Multivitamin with 1.0 mg Fluoride Chewable Tablets

supply significant amounts of Vitamins A, C, D, E, thiamine, riboflavin, niacin, vitamin B 6, vitamin B 12, and folate to supplement the diet, and to help assure that nutritional deficiencies of these vitamins will not develop. Thus, in a single easy-to-use preparation, children obtain ten essential vitamins and the important mineral, fluoride.

The American Academy of Pediatrics recommends that children up to age 16, in areas where drinking water contains less than optimal levels of fluoride, receive daily fluoride supplements.

Children using

Multivitamin with 1.0 mg Fluoride Chewable Tablets

regularly should receive semiannual dental examinations. The regular brushing of teeth and attention to good oral hygiene practices are also essential.

Multivitamin with Fluoride Chewable Tablets is a prescription product for the clinical dietary management of the metabolic processes of caries prophylaxis and provides supplementation of the diet with ten essential vitamins.

WARNING

Keep out of the reach of children. In case of accidental overdose, seek professional assistance or contact a Poison Control Center immediately.

Caution: Do not eat or drink dairy products within one hour of fluoride administration.

Should be chewed. This product, as all chewable tablets, is not recommended for children under age 4 due to risk of choking.

PRECAUTION

The suggested dose of

Multivitamin with 1.0 mg Fluoride Chewable Tablets

should not be exceeded, since dental fluorosis may result from continued ingestion of large amounts of fluoride.

Before prescribing

Multivitamin with 1.0 mg Fluoride Chewable Tablets:

1. Determine the fluoride content of the drinking water from all major sources.

2. Make sure the child is not receiving significant amounts of fluoride from other sources such as medications and swallowed toothpaste.

3. Periodically check to make sure that the child does not develop significant dental fluorosis.

ADVERSE REACTIONS

Allergic rash and other idiosyncrasies have been rarely reported.

DOSAGE AND ADMINISTRATION

One tablet daily, to be dissolved in the mouth or chewed before swallowing. Do not give a chewable tablet to a child younger than 4 years old.

HOW SUPPLIED

Product: 50090-4475

NDC: 50090-4475-0 100 TABLET, CHEWABLE in a BOTTLE, PLASTIC

STORAGE

Store at 20°-25°C (68°-77°F); excursions permitted to 15°-30°C (59°-86°F). See USP Controlled Room Temperature.

Dispense in a tight, light resistant container with a child-resistant closure as defined in the USP/NF. All prescription substitutions using this product shall be pursuant to state statutes as applicable. This is not an Orange Book product.